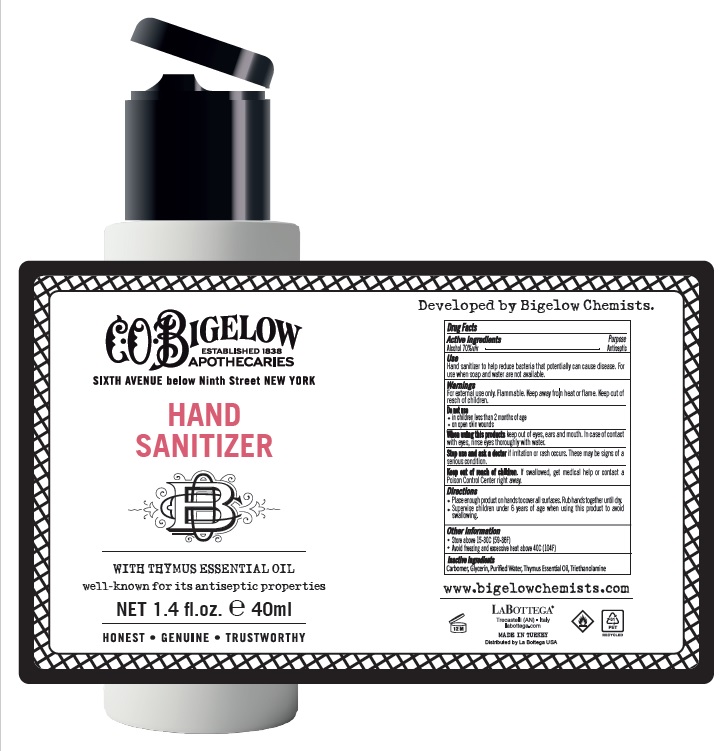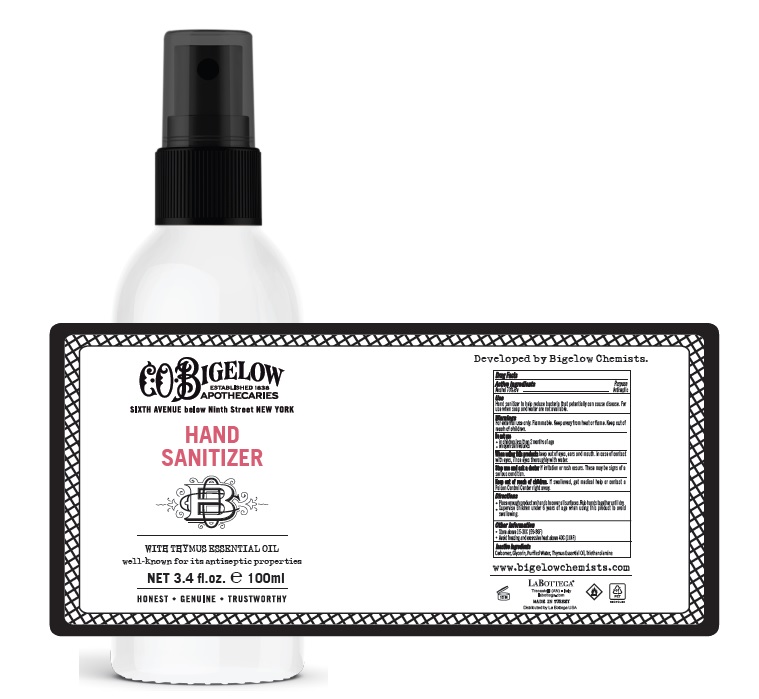 DRUG LABEL: C.O.BIGELOW HAND SANITIZER
NDC: 80176-003 | Form: GEL
Manufacturer: CERCI KOZMETIK VE OTEL EKIPMANLARI PAZARLAMA IC VE DIS TICARET LIMITED SIRKETI
Category: otc | Type: HUMAN OTC DRUG LABEL
Date: 20231026

ACTIVE INGREDIENTS: ALCOHOL 70 mL/100 mL
INACTIVE INGREDIENTS: WATER; GLYCERIN; CARBOMER HOMOPOLYMER TYPE C; TROLAMINE; HUMAN THYMUS

Drug Facts

Active Ingredient

Alcohol 70% v/v.

Purpose

Antiseptic

Use

Hand Sanitizer to help reduce bacteria that potentially can cause disease. For use when soap and water are not available.

Warnings

For external use only. Flammable. Keep out of reach of children.

Do not use

- in children less than 2 months of age
- on open skin wounds

WHEN USING

When using this products keepout of eyes, ears, and mouth. In case of contact with eyes, rinse eyes thoroughly with water.

Stop use and ask a doctor ifirritation or rash occurs. These may be signs of a serious condition.

Keep out of reach of children. If swallowed, get medical help or contact a Poison Control Center right away.

Directions

- Place enough product on hands to cover all surfaces. Rub hands together until dry.
- Supervise children under 6 years of age when using this product to avoid swallowing.

Other information

- Store between 15-30C (59-86F)
- Avoid freezing and excessive heat above 40C (104F)

Inactive ingredients

Carbomer, Glycerin, Purified Water, Thymus Essential Oil, Triethanolamine